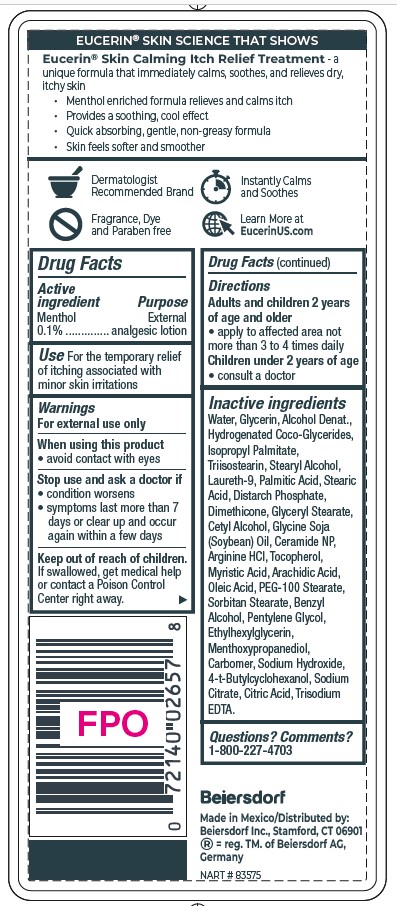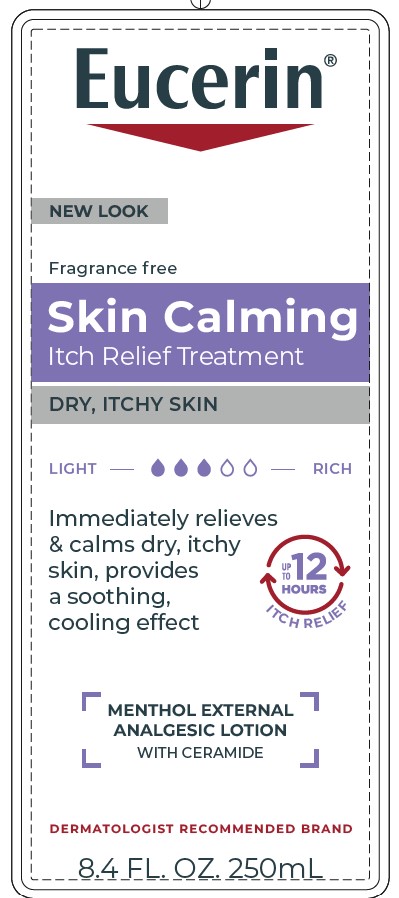 DRUG LABEL: Eucerin Skin Calming Itch Relief Treatment
NDC: 10356-357 | Form: LOTION
Manufacturer: Beiersdorf Inc
Category: otc | Type: HUMAN OTC DRUG LABEL
Date: 20251231

ACTIVE INGREDIENTS: MENTHOL 0.1 g/100 mL
INACTIVE INGREDIENTS: GLYCERYL STEARATE; SORBITAN STEARATE; MENTHOXYPROPANEDIOL; TRISODIUM EDTA; HYDROGENATED COCO-GLYCERIDES; PENTYLENE GLYCOL; SOYBEAN OIL; ETHYLHEXYLGLYCERIN; ISOPROPYL PALMITATE; TRIISOSTEARIN; LAURETH-9; STEARIC ACID; ARACHIDIC ACID; WATER; GLYCERIN; OLEIC ACID; CETYL ALCOHOL; SODIUM CITRATE; CITRIC ACID MONOHYDRATE; BENZYL ALCOHOL; ARGININE HCL; PEG-100 STEARATE; CERAMIDE NP; ALCOHOL; STEARYL ALCOHOL; TOCOPHEROL; MYRISTIC ACID; CARBOMER; PALMITIC ACID

Eucerin Skin Calming Itch Releif Treatment

ACTIVE INGREDIENT

Menthol 0.1%

PURPOSE

External analgesic lotion

INDICATIONS AND USAGE

Use for the temporary relief of itching associated with minor skin irritations.

WARNINGS

For external use only.

When using this product avoid contact with eyes.

Stop use and ask a doctor if

- condition worsens
- symptoms last more than 7 days or clear up and occur again within a few days
- irritation occurs

Keep out of reach of children. If swallowed, get medical help or contact a Poison Control Center right away.

Questions or comments 1 800 227 4703

Inactive Ingredients
Water, Glycerin, Alcohol Denat.,
Hydrogenated Coco-Glycerides,
Isopropyl Palmitate,
Triisostearin, Stearyl Alcohol,
Laureth-9, Palmitic Acid, Stearic
Acid, Distarch Phosphate,
Dimethicone, Glyceryl Stearate,
Cetyl Alcohol, Glycine Soja
(Soybean) Oil, Ceramide NP,
Arginine HCl, Tocopherol,
Myristic Acid, Arachidic Acid,
Oleic Acid, PEG-100 Stearate,
Sorbitan Stearate, Benzyl
Alcohol, Pentylene Glycol,
Ethylhexylglycerin,
Menthoxypropanediol,
Carbomer, Sodium Hydroxide,
4-t-Butylcyclohexanol, Sodium
Citrate, Citric Acid, Trisodium
EDTA.

Directions

Adults and children 8 years of age and older

- apply to affected area not more than 3 to 4 times daily

Children under 8 years of age
consult a doctor

PACKAGE LABEL

Eucerin

Fragrance Free

Skin Calming Itch Relief Treatment

Dry, Itchy Skin

Immediately relieves and calms dry, itchy skin

provides a soothing cooling effect
Menthol External Analgesic Lotion

with Ceramide

Dermatologist Recommended Brand